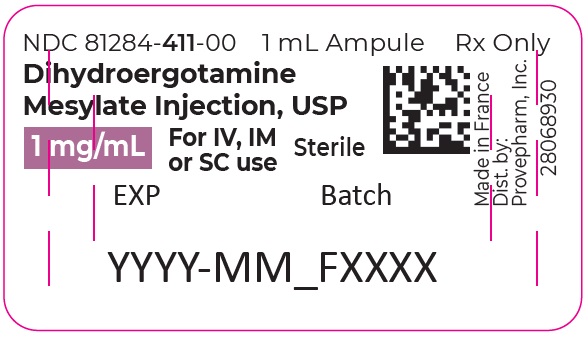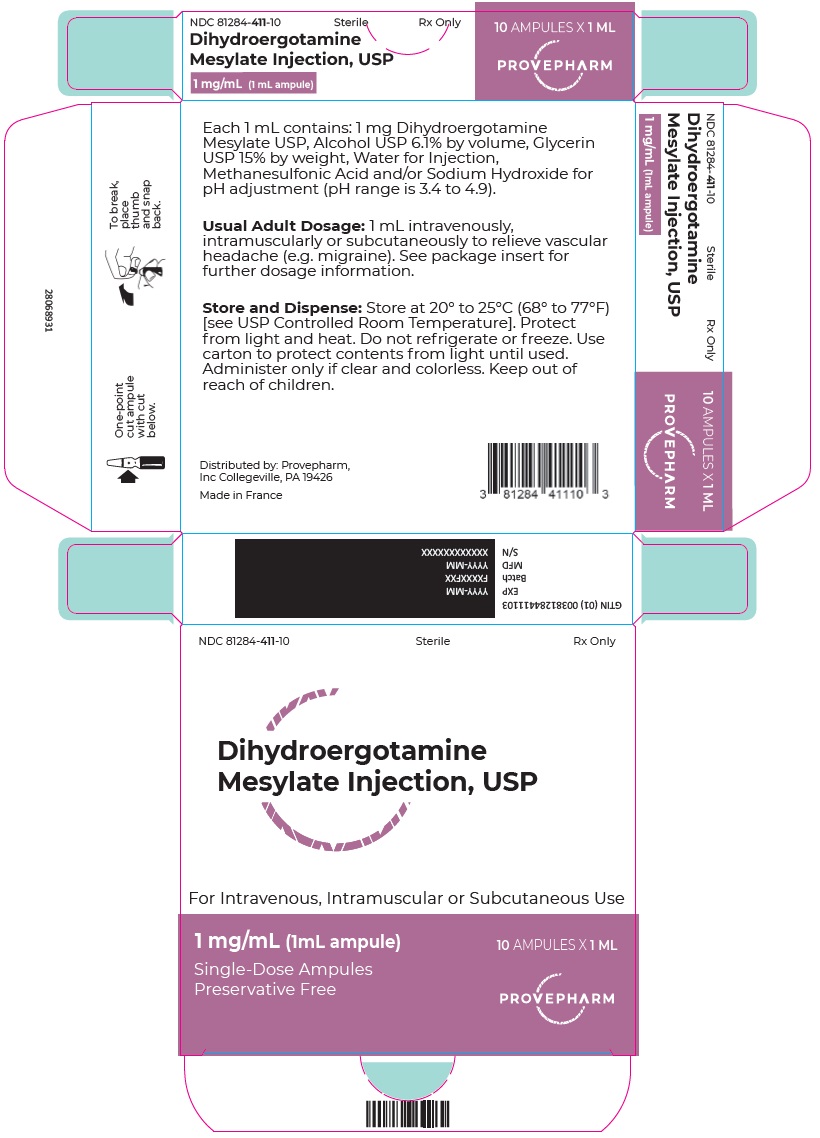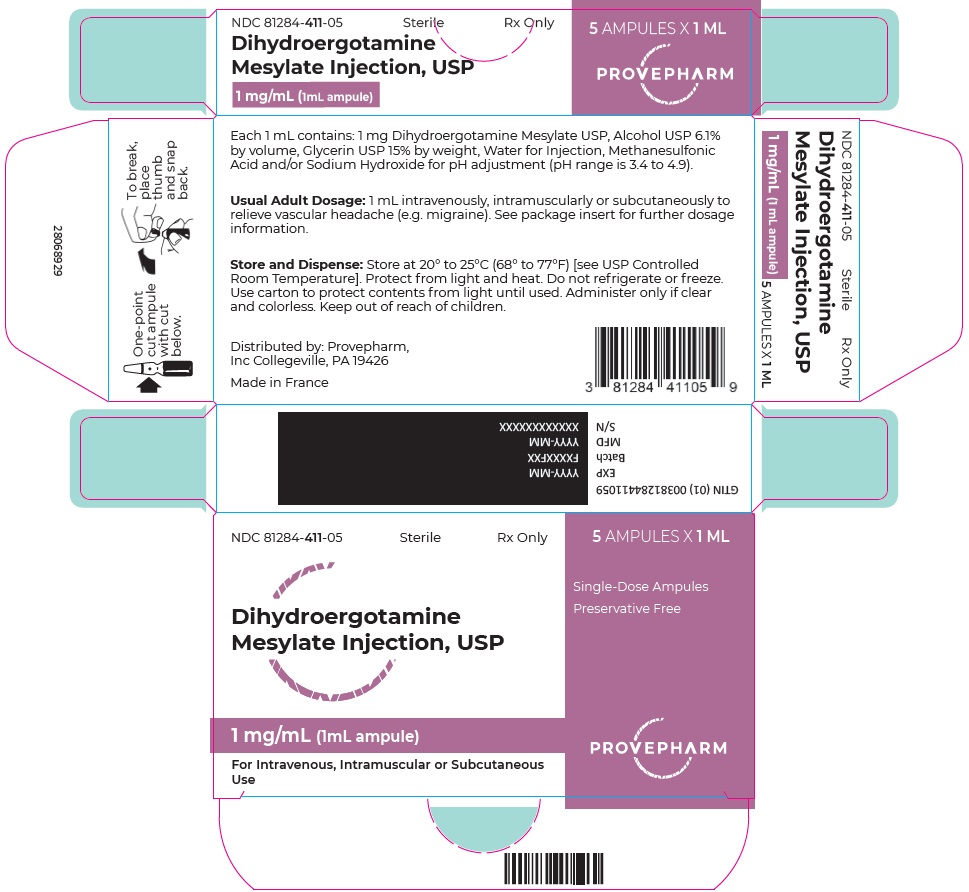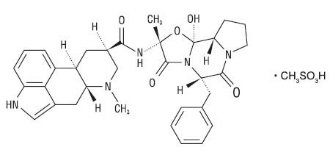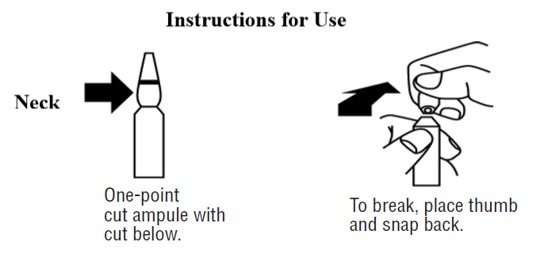 DRUG LABEL: Dihydroergotamine Mesylate
NDC: 81284-411 | Form: INJECTION, SOLUTION
Manufacturer: Provepharm Inc.
Category: prescription | Type: HUMAN PRESCRIPTION DRUG LABEL
Date: 20250225

ACTIVE INGREDIENTS: DIHYDROERGOTAMINE MESYLATE 1 mg/1 mL
INACTIVE INGREDIENTS: ALCOHOL; GLYCERIN; WATER; METHANESULFONIC ACID; SODIUM HYDROXIDE

Dihydroergotamine Mesylate Injection, USP

Rx only

WARNING: PERIPHERAL ISCHEMIA FOLLOWING COADMINISTRATION WITH POTENT CYP3A4 INHIBITORS

Serious and/or life-threatening peripheral ischemia has been associated with the coadministration of dihydroergotamine with potent CYP3A4 inhibitors including protease inhibitors and macrolide antibiotics. Because CYP3A4 inhibition elevates the serum levels of dihydroergotamine, the risk for vasospasm leading to cerebral ischemia and/or ischemia of the extremities is increased. Hence, concomitant use of these medications is contraindicated (see also CONTRAINDICATIONS and WARNINGS).

DESCRIPTION

Dihydroergotamine Mesylate Injection, USP is ergotamine hydrogenated in the 9, 10 position as the mesylate salt. Dihydroergotamine Mesylate Injection, USP is known chemically as ergotaman-3´,6´,18-trione,9,10-dihydro-12´-hydroxy-2´-methyl-5´-(phenylmethyl)-,(5´α)-, monomethanesulfonate. Its molecular weight is 679.80 and its empirical formula is C33H37N5O5•CH4O3S.

The chemical structure is:

Dihydroergotamine mesylate
C33H37N5O5•CH4O3S Mol. Wt. 679.80

Dihydroergotamine Mesylate Injection, USP is a clear, colorless solution supplied in sterile ampules for intravenous, intramuscular, or subcutaneous administration. Each mL contains 1 mg Dihydroergotamine Mesylate, USP; Alcohol, USP 6.1% by volume; Glycerin, USP 15% by weight; Water for Injection, USP; Methanesulfonic Acid and/or Sodium Hydroxide for pH adjustment (pH range is 3.4 to 4.9).

CLINICAL PHARMACOLOGY

Mechanism of Action

Dihydroergotamine binds with high affinity to 5-HT1Dα and 5-HT1Dβ receptors. It also binds with high affinity to serotonin 5-HT1A, 5-HT2A, and 5-HT2C receptors, noradrenaline α2A, α2B and α1 receptors, and dopamine D2Land D3 receptors.

The therapeutic activity of dihydroergotamine in migraine is generally attributed to the agonist effect at 5-HT1D receptors. Two current theories have been proposed to explain the efficacy of 5-HT1D receptor agonists in migraine. One theory suggests that activation of 5-HT1D receptors located on intracranial blood vessels, including those on arteriovenous anastomoses, leads to vasoconstriction, which correlates with the relief of migraine headache. The alternative hypothesis suggests that activation of 5-HT1D receptors on sensory nerve endings of the trigeminal system results in the inhibition of pro-inflammatory neuropeptide release.

In addition, dihydroergotamine possesses oxytocic properties.

Pharmacokinetics

Absorption

Absolute bioavailability for the subcutaneous and intramuscular route have not been determined; however, no difference was observed in dihydroergotamine bioavailability from intramuscular and subcutaneous doses.

Dihydroergotamine mesylate is poorly bioavailable following oral administration.

Distribution

Dihydroergotamine mesylate is 93% plasma protein bound. The apparent steady-state volume of distribution is approximately 800 liters.

Metabolism

Four dihydroergotamine mesylate metabolites have been identified in human plasma following oral administration. The major metabolite, 8´-β-hydroxydihydroergotamine, exhibits affinity equivalent to its parent for adrenergic and 5-HT receptors and demonstrates equivalent potency in several venoconstrictor activity models, in vivo and in vitro. The other metabolites, (i.e., dihydrolysergic acid, dihydrolysergic amide) and a metabolite formed by oxidative opening of the proline ring are of minor importance. Following nasal administration, total metabolites represent only 20% to 30% of plasma AUC. Quantitative pharmacokinetic characterization of the four metabolites has not been performed.

Excretion

The major excretory route of dihydroergotamine is via the bile in the feces. The total body clearance is 1.5 L/min which reflects mainly hepatic clearance. Only 6% to 7% of unchanged dihydroergotamine is excreted in the urine after intramuscular injection. The renal clearance (0.1 L/min) is unaffected by the route of dihydroergotamine administration. The decline of plasma dihydroergotamine after intramuscular or intravenous administration is multi-exponential with a terminal half-life of about 9 hours.

Subpopulations

No studies have been conducted on the effect of renal or hepatic impairment, gender, race, or ethnicity on dihydroergotamine pharmacokinetics. Dihydroergotamine Mesylate Injection, USP is contraindicated in patients with severely impaired hepatic or renal function (see CONTRAINDICATIONS).

Interactions

Pharmacokinetic interactions have been reported in patients treated orally with other ergot alkaloids (e.g., increased levels of ergotamine) and macrolide antibiotics, principally troleandomycin, presumably due to inhibition of cytochrome P4503A metabolism of the alkaloids by troleandomycin.

Dihydroergotamine has also been shown to be an inhibitor of cytochrome P4503A catalyzed reactions and rare reports of ergotism have been obtained from patients treated with dihydroergotamine and macrolide antibiotics (e.g., troleandomycin, clarithromycin, erythromycin), and in patients treated with dihydroergotamine and protease inhibitors (e.g., ritonavir), presumably due to inhibition of cytochrome P4503A metabolism of ergotamine (see CONTRAINDICATIONS). No pharmacokinetic interactions involving other cytochrome P450 isoenzymes are known.

INDICATIONS AND USAGE

Dihydroergotamine Mesylate Injection, USP is indicated for the acute treatment of migraine headaches with or without aura and the acute treatment of cluster headache episodes.

CONTRAINDICATIONS

There have been a few reports of serious adverse events associated with the coadministration of dihydroergotamine and potent CYP3A4 inhibitors, such as protease inhibitors and macrolide antibiotics, resulting in vasospasm that led to cerebral ischemia and/or ischemia of the extremities. The use of potent CYP3A4 inhibitors (i.e., ritonavir, nelfinavir, indinavir, erythromycin, clarithromycin, troleandomycin, ketoconazole, itraconazole) with dihydroergotamine is, therefore, contraindicated (see WARNINGS, CYP3A4 Inhibitors).

Dihydroergotamine Mesylate Injection, USP should not be given to patients with ischemic heart disease (e.g., angina pectoris, history of myocardial infarction, or documented silent ischemia) or to patients who have clinical symptoms or findings consistent with coronary artery vasospasm including Prinzmetal's variant angina (see WARNINGS).

Because Dihydroergotamine Mesylate Injection, USP may increase blood pressure, it should not be given to patients with uncontrolled hypertension.

Dihydroergotamine Mesylate Injection, USP, 5-HT1 agonists (e.g., sumatriptan), ergotamine-containing or ergot-type medications or methysergide should not be used within 24 hours of each other.

Dihydroergotamine Mesylate Injection, USP should not be administered to patients with hemiplegic or basilar migraine.

In addition to those conditions mentioned above, Dihydroergotamine Mesylate Injection, USP is also contraindicated in patients with known peripheral arterial disease, sepsis, following vascular surgery and severely impaired hepatic or renal function.

Dihydroergotamine Mesylate Injection, USP is contraindicated in patients who have previously shown hypersensitivity to ergot alkaloids.

Dihydroergotamine mesylate should not be used with peripheral and central vasoconstrictors because the combination may result in additive or synergistic elevation of blood pressure.

WARNINGS

Dihydroergotamine Mesylate Injection, USP should only be used where a clear diagnosis of migraine headache has been established.

CYP3A4 Inhibitors (e.g., Macrolide Antibiotics and Protease Inhibitors)

There have been rare reports of serious adverse events in connection with the coadministration of dihydroergotamine and potent CYPA4 inhibitors, such as protease inhibitors and macrolide antibiotics, resulting in vasospasm that led to cerebral ischemia and/or and ischemia of the extremities. The use of potent CYP3A4 inhibitors with dihydroergotamine should therefore be avoided (see CONTRAINDICATIONS). Examples of some of the more potent CYP3A4 inhibitors include: antifungals ketoconazole and itraconazole, the protease inhibitors ritonavir, nelfinavir, and indinavir, and macrolide antibiotics erythromycin, clarithromycin, and troleandomycin. Other less potent CYP3A4 inhibitors should be administered with caution. Less potent inhibitors include saquinavir, nefazodone, fluconazole, grapefruit juice, fluoxetine, fluvoxamine, zileuton, and clotrimazole. These lists are not exhaustive, and the prescriber should consider the effects on CYP3A4 of other agents being considered for concomitant use with dihydroergotamine.

Fibrotic Complications

There have been reports of pleural and retroperitoneal fibrosis in patients following prolonged daily use of injectable dihydroergotamine mesylate. Rarely, prolonged daily use of other ergot alkaloid drugs has been associated with cardiac valvular fibrosis. Rare cases have also been reported in association with the use of injectable dihydroergotamine mesylate; however, in those cases, patients also received drugs known to be associated with cardiac valvular fibrosis.

Administration of Dihydroergotamine Mesylate Injection, USP, should not exceed the dosing guidelines and should not be used for chronic daily administration (see DOSAGE AND ADMINISTRATION).

Risk of Myocardial Ischemia and/or Infarction and Other Adverse Cardiac Events

Dihydroergotamine Mesylate Injection, USP should not be used by patients with documented ischemic or vasospastic coronary artery disease (see CONTRAINDICATIONS). It is strongly recommended that Dihydroergotamine Mesylate Injection, USP not be given to patients in whom unrecognized coronary artery disease (CAD) is predicted by the presence of risk factors (e.g., hypertension, hypercholesterolemia, smoker, obesity, diabetes, strong family history of CAD, females who are surgically or physiologically postmenopausal, or males who are over 40 years of age) unless a cardiovascular evaluation provides satisfactory clinical evidence that the patient is reasonably free of coronary artery and ischemic myocardial disease or other significant underlying cardiovascular disease. The sensitivity of cardiac diagnostic procedures to detect cardiovascular disease or predisposition to coronary artery vasospasm is modest, at best. If, during the cardiovascular evaluation, the patient's medical history or electrocardiographic investigations reveal findings indicative of or consistent with coronary artery vasospasm or myocardial ischemia, Dihydroergotamine Mesylate Injection, USP should not be administered (see CONTRAINDICATIONS).

For patients with risk factors predictive of CAD who are determined to have a satisfactory cardiovascular evaluation, it is strongly recommended that administration of the first dose of Dihydroergotamine Mesylate Injection, USP take place in the setting of a physician's office or similar medically staffed and equipped facility unless the patient has previously received dihydroergotamine mesylate. Because cardiac ischemia can occur in the absence of clinical symptoms, consideration should be given to obtaining on the first occasion of use, an electrocardiogram (ECG) during the interval immediately following Dihydroergotamine Mesylate Injection, USP in those patients with risk factors.

It is recommended that patients who are intermittent long-term users of Dihydroergotamine Mesylate Injection, USP and who have or acquire risk factors predictive of CAD, as described above, undergo periodic interval cardiovascular evaluation as they continue to use Dihydroergotamine Mesylate Injection, USP.

The systematic approach described above is currently recommended as a method to identify patients in whom Dihydroergotamine Mesylate Injection, USP may be used to treat migraine headaches with an acceptable margin of cardiovascular safety.

Cardiac Events and Fatalities

The potential for adverse cardiac events exists. Serious adverse cardiac events, including acute myocardial infarction, life-threatening disturbances of cardiac rhythm, and death have been reported to have occurred following the administration of dihydroergotamine mesylate injection. Considering the extent of use of dihydroergotamine mesylate in patients with migraine, the incidence of these events is extremely low.

Drug-Associated Cerebrovascular Events and Fatalities

Cerebral hemorrhage, subarachnoid hemorrhage, stroke, and other cerebrovascular events have been reported in patients treated with Dihydroergotamine Mesylate Injection, USP; and some have resulted in fatalities. In a number of cases, it appears possible that the cerebrovascular events were primary, the Dihydroergotamine Mesylate Injection, USP having been administered in the incorrect belief that the symptoms experienced were a consequence of migraine, when they were not. It should be noted that patients with migraine may be at increased risk of certain cerebrovascular events (e.g., stroke, hemorrhage, transient ischemic attack).

Other Vasospasm-Related Events

Dihydroergotamine Mesylate Injection, USP, like other ergot alkaloids, may cause vasospastic reactions other than coronary artery vasospasm. Myocardial, peripheral vascular, and colonic ischemia have been reported with Dihydroergotamine Mesylate Injection, USP.

Dihydroergotamine Mesylate Injection, USP associated vasospastic phenomena may also cause muscle pains, numbness, coldness, pallor, and cyanosis of the digits. In patients with compromised circulation, persistent vasospasm may result in gangrene or death. Dihydroergotamine Mesylate Injection, USP should be discontinued immediately if signs or symptoms of vasoconstriction develop.

Increase in Blood Pressure

Significant elevation in blood pressure has been reported on rare occasions in patients with and without a history of hypertension treated with dihydroergotamine mesylate injection. Dihydroergotamine Mesylate Injection, USP is contraindicated in patients with uncontrolled hypertension (see CONTRAINDICATIONS).

An 18% increase in mean pulmonary artery pressure was seen following dosing with another 5-HT1 agonist in a study evaluating subjects undergoing cardiac catheterization.

Medication Overuse Headache

Overuse of acute migraine drugs (e.g., ergotamines, triptans, opioids, or a combination of these drugs for 10 or more days per month) may lead to exacerbation of headache (i.e., medication overuse headache). Medication overuse headache may present as migraine-like daily headaches or as a marked increase in frequency of migraine attacks. Detoxification of patients including withdrawal of the overused drugs and treatment of withdrawal symptoms (which often includes a transient worsening of headache) may be necessary.

Preterm Labor

Based on the mechanism of action of dihydroergotamine and findings from the published literature, Dihydroergotamine Mesylate Injection, USP may cause preterm labor. Avoid use of Dihydroergotamine Mesylate Injection, USP during pregnancy (see PRECAUTIONS).

PRECAUTIONS

General

Dihydroergotamine Mesylate Injection, USP may cause coronary artery vasospasm; patients who experience signs or symptoms suggestive of angina following its administration should, therefore, be evaluated for the presence of CAD or a predisposition to variant angina before receiving additional doses. Similarly, patients who experience other symptoms or signs suggestive of decreased arterial flow, such as ischemic bowel syndrome or Raynaud's syndrome following the use of any 5-HT agonist are candidates for further evaluation (see WARNINGS).

Information for Patients

The text of a patient information sheet is printed at the end of this insert. To assure safe and effective use of Dihydroergotamine Mesylate Injection, USP, the information and instructions provided in the patient information sheet should be discussed with patients.

Patients should be advised to report to the physician immediately any of the following: numbness or tingling in the fingers and toes, muscle pain in the arms and legs, weakness in the legs, pain in the chest, temporary speeding or slowing of the heart rate, swelling, or itching.

Prior to the initial use of the product by a patient, the prescriber should take steps to ensure that the patient understands how to use the product as provided (see Patient Information Sheet and product packaging).

Administration of Dihydroergotamine Mesylate Injection, USP should not exceed the dosing guidelines and should not be used for chronic daily administration (see DOSAGE AND ADMINISTRATION).

Drug Interactions

Vasoconstrictors

Dihydroergotamine Mesylate Injection, USP should not be used with peripheral vasoconstrictors because the combination may cause synergistic elevation of blood pressure.

Sumatriptan

Sumatriptan has been reported to cause coronary artery vasospasm, and its effect could be additive with Dihydroergotamine Mesylate Injection, USP. Sumatriptan and Dihydroergotamine Mesylate Injection, USP should not be taken within 24 hours of each other (see CONTRAINDICATIONS).

Beta Blockers

Although the results of a clinical study did not indicate a safety problem associated with the administration of Dihydroergotamine Mesylate Injection, USP to subjects already receiving propranolol, there have been reports that propranolol may potentiate the vasoconstrictive action of ergotamine by blocking the vasodilating property of epinephrine.

Nicotine

Nicotine may provoke vasoconstriction in some patients, predisposing to a greater ischemic response to ergot therapy.

CYP3A4 Inhibitors (e.g., Macrolide Antibiotics and Protease Inhibitors) (see CONTRAINDICATIONSand WARNINGS)

SSRI's

Weakness, hyperreflexia, and incoordination have been reported rarely when 5-HT1 agonists have been co-administered with SSRI's (e.g., fluoxetine, fluvoxamine, paroxetine, sertraline). There have been no reported cases from spontaneous reports of drug interaction between SSRI's and Dihydroergotamine Mesylate Injection, USP.

Oral Contraceptives

The effect of oral contraceptives on the pharmacokinetics of Dihydroergotamine Mesylate Injection, USP has not been studied.

Carcinogenesis, Mutagenesis, Impairment of Fertility

Carcinogenesis

In a 2-year mouse carcinogenicity study, subcutaneous (SC) administration of dihydroergotamine mesylate (0, 0.5, 1.5 or 5 mg/kg/day) resulted in an increased incidence of fibrosarcoma at the injection sites in males and females at the high dose. The higher dose not associated with an increase in tumors (1.5 mg/kg/day) is approximately 2 times the recommended human dose (RHD) of 3 mg/day SC on a body surface area (mg/m^2) basis.

In a 2-year rat carcinogenicity study, intranasal administration of dihydroergotamine mesylate (0, 0.4, 0.8 or 1.6 mg/day for 13 weeks, followed by 0, 0.08, 0.24 or 0.8 mg/day for the remainder of the study) did not result in an increase in tumors.

Mutagenesis

Dihydroergotamine mesylate was clastogenic in two in vitro chromosomal aberration assays, the V79 Chinese hamster cell assay with metabolic activation and the cultured human peripheral blood lymphocyte assay. There was no evidence of mutagenic potential when dihydroergotamine mesylate was tested in the presence or absence of metabolic activation in two gene mutation assays (the Ames test and the in vitro mammalian Chinese hamster V79/HGPRT assay) and in an assay for DNA damage (the rat hepatocyte unscheduled DNA synthesis test). Dihydroergotamine was not clastogenic in the in vivo mouse and hamster micronucleus tests.

Impairment of Fertility

Intranasal administration of dihydroergotamine to rats at doses up to 1.6 mg/day was not associated with adverse effects on fertility.

Pregnancy

Risk Summary

Available data from published literature indicated an increased risk of preterm delivery with Dihydroergotamine Mesylate Injection, USP use during pregnancy. Avoid use of Dihydroergotamine Mesylate Injection, USP during pregnancy (see WARNINGS). Data collected over decades have shown no increased risk of major birth defects or miscarriage with the use of dihydroergotamine mesylate during pregnancy.

In animal reproduction studies, adverse effects on development were observed following intranasal administration of dihydroergotamine mesylate during pregnancy (decreased fetal body weight and/or skeletal ossification) in rats and rabbits or during pregnancy and lactation in rats (decreased body weight and impaired reproductive function in the offspring) at doses that were not associated with maternal toxicity (see Data).

The estimated rate of major birth defects (2.2% to 2.9%) and miscarriage (17%) among deliveries to women with migraine are similar to rates reported in women without migraine. All pregnancies have a background risk of birth defect, loss, or other adverse outcomes. In the U.S. general population, the estimated background risk of major birth defects and miscarriages in clinically recognized pregnancies is 2% to 4% and 15% to 20%, respectively.

Data

Animal Data

Intranasal administration of dihydroergotamine mesylate to pregnant rats throughout the period of organogenesis resulted in decreased fetal body weight and/or skeletal ossification at doses of 0.16 mg/day and greater. A no-effect level for adverse effects on embryofetal development was not identified in rats. Intranasal administration of dihydroergotamine mesylate to pregnant rabbits throughout organogenesis resulted in decreased skeletal ossification of 3.6 mg/day. The no-effect dose for adverse effects on embryofetal development in rabbits was 1.2 mg/day.

Intranasal administration of dihydroergotamine mesylate to female rats throughout pregnancy and lactation resulted in decreased body weight and impaired reproductive function (decreased mating indices) in the offspring at doses of 0.16 mg/day or greater. A no-effect dose for adverse effects on pre- and postnatal development in rats was not established. Effects on offspring development occurred at doses below those that produced evidence of maternal toxicity in these studies.

Dihydroergotamine-induced intrauterine growth retardation has been attributed to reduced uteroplacental blood flow resulting from prolonged vasoconstriction of the uterine vessels and/or increased myometrial tone.

Nursing Mothers

Risk Summary

There are no data on the presence of dihydroergotamine in human milk; however, ergotamine, a related drug, is present in human milk. There are reports of vomiting, diarrhea, weak pulse, and unstable blood pressure in breastfed infants exposed to ergotamine. Dihydroergotamine Mesylate Injection, USP may reduce milk supply because it may decrease prolactin levels.

Because of the potential for reduced milk supply and serious adverse events in the breastfed infant, including diarrhea, vomiting weak pulse, and unstable blood pressure, advise patients not to breastfeed during treatment with Dihydroergotamine Mesylate Injection, USP and for 3 days after the last dose. Breast milk supply during this time should be pumped and discarded.

Pediatric Use

Safety and effectiveness in pediatric patients have not been established.

ADVERSE REACTIONS

Serious cardiac events, including some that have been fatal, have occurred following use of Dihydroergotamine Mesylate Injection, USP, but are extremely rare. Events reported have included coronary artery vasospasm, transient myocardial ischemia, myocardial infarction, ventricular tachycardia, and ventricular fibrillation (see CONTRAINDICATIONS, WARNINGS, and PRECAUTIONS). Fibrotic complications have been reported in association with long term use of injectable dihydroergotamine mesylate (see WARNINGS, Fibrotic Complications).

Post-introduction Reports

The following events derived from postmarketing experience have been occasionally reported in patients receiving Dihydroergotamine Mesylate Injection, USP: vasospasm, paraesthesia, hypertension, dizziness, anxiety, dyspnea, headache, flushing, diarrhea, rash, increased sweating, and pleural and retroperitoneal fibrosis after long-term use of dihydroergotamine. Extremely rare cases of myocardial infarction and stroke have been reported. A causal relationship has not been established.

Dihydroergotamine Mesylate Injection, USP is not recommended for prolonged daily use (see DOSAGE AND ADMINISTRATION).

To report SUSPECTED ADVERSE REACTIONS, contact Provepharm Inc., at 1–833-727-6556 or safety-us@provepharm.com or FDA at 1-800-FDA-1088 or www.fda.gov/medwatch.

DRUG ABUSE AND DEPENDENCE

Currently available data have not demonstrated drug abuse or psychological dependence with dihydroergotamine. However, cases of drug abuse and psychological dependence in patients on other forms of ergot therapy have been reported. Thus, due to the chronicity of vascular headaches, it is imperative that patients be advised not to exceed recommended dosages.

OVERDOSAGE

To date, there have been no reports of acute overdosage with this drug. Due to the risk of vascular spasm, exceeding the recommended dosages of Dihydroergotamine Mesylate Injection, USP is to be avoided. Excessive doses of dihydroergotamine may result in peripheral signs and symptoms of ergotism. Treatment includes discontinuance of the drug, local application of warmth to the affected area, the administration of vasodilators, and nursing care to prevent tissue damage.

In general, the symptoms of an acute Dihydroergotamine Mesylate Injection, USP overdose are similar to those of an ergotamine overdose, although there is less pronounced nausea and vomiting with Dihydroergotamine Mesylate Injection, USP. The symptoms of an ergotamine overdose include the following: numbness, tingling, pain, and cyanosis of the extremities associated with diminished or absent peripheral pulses; respiratory depression; an increase and/or decrease in blood pressure, usually in that order; confusion, delirium, convulsions, and coma; and/or some degree of nausea, vomiting, and abdominal pain.

In laboratory animals, significant lethality occurs when dihydroergotamine is given at I.V. doses of 44 mg/kg in mice, 130 mg/kg in rats, and 37 mg/kg in rabbits.

Up-to-date information about the treatment of overdosage can often be obtained from a certified Regional Poison Control Center. Telephone numbers of certified Poison Control Centers are listed in the Physician's Desk Reference (PDR)*.

DOSAGE AND ADMINISTRATION

Dihydroergotamine Mesylate Injection, USP should be administered in a dose of 1 mL intravenously, intramuscularly or subcutaneously. The dose can be repeated, as needed, at 1-hour intervals to a total dose of 3 mL for intramuscular or subcutaneous delivery or 2 mL for intravenous delivery in a 24-hour period. The total weekly dosage should not exceed 6 mL. Dihydroergotamine Mesylate Injection, USP should not be used for chronic daily administration.

HOW SUPPLIED/STORAGE AND HANDLING

Dihydroergotamine Mesylate Injection, USP

Available as a clear, colorless, sterile solution in single 1 mL sterile ampules containing 1 mg of dihydroergotamine mesylate per mL, in packages of 5 (NDC 81284-411-05) and 10 (NDC 81284-411-10).

STORAGE AND HANDLING

Store at 20°C to 25°C (68°F to 77°F); excursions permitted between 15°C to 30°C (59°F to 86°F) [see USP Controlled Room Temperature]. Use carton to protect contents from light until used.

Do not refrigerate or freeze.

To assure constant potency, protect the ampules from light and heat. Administer only if clear and colorless.

*Trademark of PDR Network, LLC

Manufactured for:
Provepharm SAS

Distributed by:
Provepharm, Inc.
Collegeville, PA 19426

Made in France

Revised: 11/2022

INSTRUCTION FOR PATIENTS ON SUBCUTANEOUS SELF-INJECTION

Information for the Patient

Dihydroergotamine Mesylate Injection, USP

Before self-injecting Dihydroergotamine Mesylate Injection, USP by subcutaneous administration, you will need to obtain professional instruction on how to properly administer your medication. Below are some of the steps you should follow carefully. Read this leaflet completely before using this medication.

This leaflet does not contain all of the information on Dihydroergotamine Mesylate Injection, USP . Your pharmacist and/or health care provider can provide more detailed information.

Purpose of your medication

Dihydroergotamine Mesylate Injection, USP is intended to treat an active migraine headache. Do not try to use it to prevent a headache if you have no symptoms. Do not use it to treat common tension headache or a headache that is not at all typical of your usual migraine headache. Administration of Dihydroergotamine Mesylate Injection, USP should not exceed the dosing guidelines and should not be used for chronic daily administration. There have been reports of fibrosis (stiffening) in the lung or kidney areas in patients following prolonged daily use of injectable dihydroergotamine mesylate. Rarely, prolonged daily use of other ergot alkaloid drugs (the class of drugs to which Dihydroergotamine Mesylate Injection, USP belongs) has been associated with heart valvular fibrosis.

Rare cases have also been reported in association with the use of injectable dihydroergotamine mesylate; however, in those cases, patients also received drugs known to be associated with heart valvular fibrosis.

Do not use Dihydroergotamine Mesylate Injection, USP if you:

• have any disease affecting your heart, arteries, or circulation.
• are taking certain anti-HIV medications (protease inhibitors).
• are taking a macrolide antibiotic such as troleandomycin, clarithromycin or erythromycin.

Important questions to consider before using Dihydroergotamine Mesylate Injection, USP

Please answer the following questions before you use your Dihydroergotamine Mesylate Injection, USP.

If you answer YES to any of these questions or are unsure of the answer, you should talk to your doctor before using Dihydroergotamine Mesylate Injection, USP.

- Do you have high blood pressure?
- Do you have chest pain, shortness of breath, heart disease, or have you had any surgery on your heart arteries?
- Do you have risk factors for heart disease (such as high blood pressure, high cholesterol, obesity, diabetes, smoking, strong family history of heart disease, or you are postmenopausal or a male over 40)?
- Do you have any problems with blood circulation in your arms or legs, fingers, or toes?
- Are you pregnant? Do you think you might be pregnant? Are you trying to become pregnant? Are you sexually active and not using birth control?
  - Dihydroergotamine Mesylate Injection, USP may cause preterm labor. Dihydroergotamine Mesylate Injection, USP should be avoided during pregnancy. Talk to your healthcare provider right away if you are pregnant or want to become pregnant.
- Are you breast feeding?
  - Dihydroergotamine Mesylate Injection, USP may reduce breast milk supply and pass into your breast milk. Dihydroergotamine Mesylate Injection, USP may be harmful to your baby. Do not breastfeed your baby while taking Dihydroergotamine Mesylate Injection, USP and for 3 days after you use Dihydroergotamine Mesylate Injection, USP. Talk with your healthcare provider about the best way to feed your baby if you take Dihydroergotamine Mesylate Injection, USP.
- Have you ever had to stop taking this or any other medication because of an allergy or bad reaction?
- Are you taking any other migraine medications, erythromycin or other antibiotics, or medications for blood pressure prescribed by your doctor, or other medicines obtained from your drugstore without a doctor's prescription?
- Do you smoke?
- Have you had, or do you have, any disease of the liver or kidney?
- Is this headache different from your usual migraine attacks?
- Are you using Dihydroergotamine Mesylate Injection, USP or other dihydroergotamine mesylate containing drugs on a daily basis?
- Are you taking a protease inhibitor for HIV therapy?
- Are you taking a macrolide class of antibiotic?

Serious or potentially life-threatening reductions in blood flow to the brain or extremities have been reported rarely due to interactions between Dihydroergotamine Mesylate Injection, USP and protease inhibitors or macrolide antibiotics.

REMEMBER TO TELL YOUR DOCTOR IF YOU HAVE ANSWERED “YES” TO ANY OF THESE QUESTIONS BEFORE YOU USE Dihydroergotamine Mesylate Injection, USP

Side effects to watch out for

Although the following reactions rarely occur, they can be serious and should be reported to your physician immediately:

- Numbness or tingling in your fingers and toes
- Pain, tightness, or discomfort in your chest
- Muscle pain or cramps in your arms and legs
- Weakness in your legs
- Temporary speeding or slowing of your heart rate
- Swelling or itching

Dosage

Your doctor will have told you what dose to use for each migraine attack. Should you get another migraine attack in the same day as the attack you treated, you must not treat it with Dihydroergotamine Mesylate Injection, USP unless at least 6 hours have elapsed since your last injection. No more than 6 mL of Dihydroergotamine Mesylate Injection, USP should be injected during a 1-week period. Dihydroergotamine Mesylate Injection, USP is not intended to be used on a prolonged daily basis.

Learn what to do in case of an Overdose

If you have used more medication than you have been instructed, contact your doctor, hospital emergency department, or nearest poison control center immediately.

How to use the Dihydroergotamine Mesylate Injection, USP

1.Use Available Training Materials

- Read and follow the instructions in the patient instruction booklet which is provided with the Dihydroergotamine Mesylate Injection, USP package before attempting to use the product.
- If there are any questions concerning the use of your Dihydroergotamine Mesylate Injection, USP , ask your doctor or pharmacist.

2.Preparing for the Injection

- Carefully examine the ampule (glass vial) of Dihydroergotamine Mesylate Injection, USP for any cracks or breaks, and the liquid for discoloration, cloudiness, or particles. If any of these defects are present, use a new ampule, make certain it is intact, and return the defective ampule to your doctor or pharmacy. Once you open an ampule, if it is not used within an hour, it should be thrown away.

3.Locating an Injection Site

- Administer your subcutaneous injection in the middle of your thigh, well above the knee.

4.Drawing the Medication into the Syringe

1. Wash your hands thoroughly with soap and water.
2. Check the dose of your medication.
3. Look to see if there is any liquid at the top of the ampule. If there is, gently flick the ampule with your finger to get all the liquid into the bottom portion of the ampule.
4. Hold the bottom of the ampule in one hand. Clean the ampule neck with an alcohol wipe using the other hand. To break, place the alcohol wipe around the neck of the ampule and break it open by pressing your thumb against the neck of the ampule.
5. Tilt the ampule down at a 45° angle. Insert the needle into the solution in the ampule.
6. Draw up the medication by pulling back the plunger slowly and steadily until you reach your dose.
7. Check the syringe for air bubbles. Hold it with the needle pointing upward. If there are air bubbles, tap your finger against the barrel of the syringe to get the bubbles to the top. Slowly and carefully push the plunger up so that the bubbles are pushed out through the needle and you see a drop of medication.
8. When there are no air bubbles, check the dose of the medication. If the dose is incorrect, repeat steps e, f, g, and h until you draw up the right dose.

5.Preparing the Injection Site

- With a new alcohol wipe, clean the selected injection site thoroughly with a firm, circular motion from inside to outside. Wait for the injection site to dry before injecting.

6.Administering the Injection

- Hold the syringe/needle in your right hand.
- With your left hand, firmly grasp about a 1-inch fold of skin at the injection site.
- Push the needle shaft, bevel side up, all the way into the fold of skin at a 45° to 90° angle, then release the fold of skin.
- While holding the syringe with your left hand, use your right hand to draw back slightly on the plunger.
- If you do not see any blood coming back into the syringe, inject the medication by pushing down on the plunger. If you do see blood in the syringe, that means the needle has penetrated a vein. If this happens, pull the needle/syringe out of the skin slightly and draw back on the plunger again. If no blood is seen this time, inject the medication
- Use your right hand to pull the needle out of your skin quickly at the same angle you injected it. Immediately press the alcohol wipe on the injection site and rub.

Check the expiration date printed on the ampule containing medication. If the expiration date has passed, do not use it.

Answers to Patients' Questions About Dihydroergotamine Mesylate Injection, USP

What if I need help in using my Dihydroergotamine Mesylate Injection, USP?

If you have any questions or if you need help in opening, putting together, or using Dihydroergotamine Mesylate Injection, USP , speak to your doctor or pharmacist.

How much medication should I use and how often?

Your doctor will have told you what dose to use for each migraine attack. Should you get another migraine attack in the same day as the attack you treated, you must not treat it with Dihydroergotamine Mesylate Injection, USP unless at least 6 hours have elapsed since your last injection. No more than 6 mL of Dihydroergotamine Mesylate Injection, USP should be injected during a 1-week period. Do not use more than this amount unless instructed to do so by your doctor. Dihydroergotamine Mesylate Injection, USP is not intended for chronic daily use.

If you have any other unanswered questions about Dihydroergotamine Mesylate Injection, USP, consult your doctor or pharmacist.

Manufactured for:
Provepharm SAS

Distributed by:
Provepharm, Inc.
Collegeville, PA 19426

Made in France

Revised: 11/2022

PRINCIPAL DISPLAY PANEL - 1 mL Ampule Label

NDC 81284-411-00 1 mL Ampule Rx only

Dihydroergotamine
Mesylate Injection, USP

1 mg/mL For IV, IM or SC Use Sterile

PRINCIPAL DISPLAY PANEL - 5 x 1 mL Ampules Carton Label

NDC 81284-411-05 Sterile Rx only

Dihydroergotamine
Mesylate Injection, USP

1 mg/mL (1mL Ampule)

For Intravenous, Intramuscular or Subcutaneous Use

5 AMPULES X 1 ML

Single-Dose Ampules

Preservative Free

PROVEPHARM

PRINCIPAL DISPLAY PANEL - 10 x 1 mL Ampules Carton Label

NDC 81284-411-10 Sterile Rx only

Dihydroergotamine
Mesylate Injection, USP

For Intravenous, Intramuscular or Subcutaneous Use

1 mg/mL (1mL Ampule)

10 AMPULES X 1 ML

Single-Dose Ampules

Preservative Free

PROVEPHARM